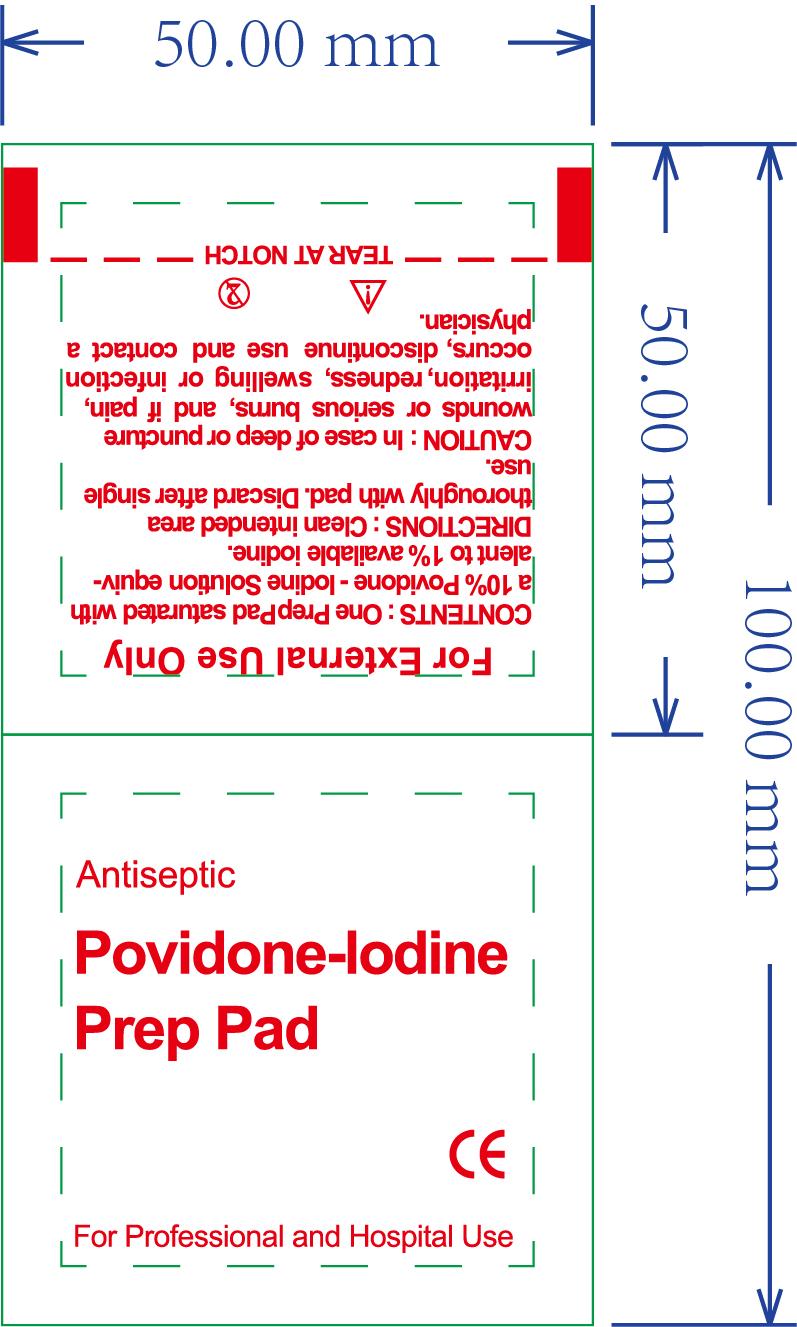 DRUG LABEL: Povidone-lodine prep pad
NDC: 84449-002 | Form: PATCH
Manufacturer: SHENZHEN BENLIJU BIO-TECH CO.,LTD
Category: otc | Type: HUMAN OTC DRUG LABEL
Date: 20260105

ACTIVE INGREDIENTS: POVIDONE-IODINE 10 mg/1 g
INACTIVE INGREDIENTS: WATER

ACTIVE INGREDIENT

Available Iodine

PURPOSE

disinfect

INDICATIONS AND USAGE

For preparation of the skin prior to an injection and to decrease germs in minor cuts and scrapes.

WARNINGS

*For extemal use only.
*Flammable. keep away from fire or flame.

Do not use " with electrocautery procedures " in the eyes. lf contact occurs, flush eyes with water.

When using this product keep out of eyes, ears, and mouth. In case of contact with eyes, rinse eyes thoroughly with water.

*Stop use if irritation and redness develop. If condition persists consult your health care practioner.

*Stop use and ask a doctor if irritation or rash occurs. These may be signs of a serious condition.

Keep out of reach of children. If swallowed, get medical help or contact a Poison Control Center right away.

DOSAGE AND ADMINISTRATION

For preparation of the skin prior to an injection and to decrease germs in minor cuts and scrapes.One piece at a time.

STORAGE AND HANDLING

Store at room temperature.

INACTIVE INGREDIENT

water